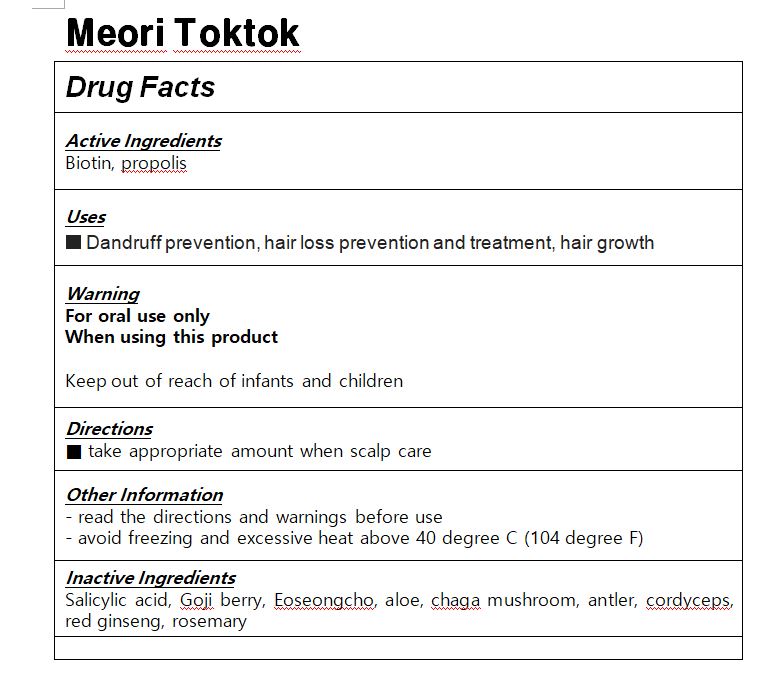 DRUG LABEL: Meori Toktok
NDC: 83125-0001 | Form: LIQUID
Manufacturer: Kolive Cell Co., Ltd.
Category: otc | Type: HUMAN OTC DRUG LABEL
Date: 20250206

ACTIVE INGREDIENTS: BIOTIN 0.5 g/100 mL; MENTHOL 0.2 g/100 mL
INACTIVE INGREDIENTS: SULFUR; WATER

Drug Facts

ACTIVE INGREDIENT

Biotin, propolis

PURPOSE

Dandruff prevention, hair loss prevention and treatment, hair growth

KEEP OUT OF REACH OF THE CHILDREN

INDICATIONS AND USAGE

take appropriate amount when scalp care

WARNINGS

Keep out of reach of infants and children

DOSAGE AND ADMINISTRATION

take appropriate amount when scalp care

INACTIVE INGREDIENT

Salicylic acid, Goji berry, Eoseongcho, aloe, chaga mushroom, antler, cordyceps, red ginseng, rosemary